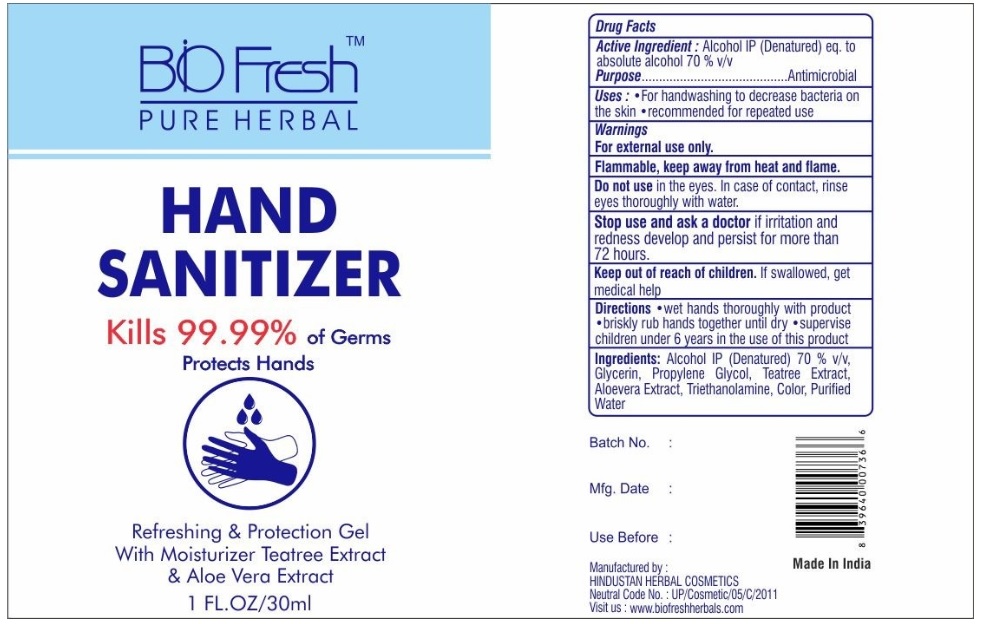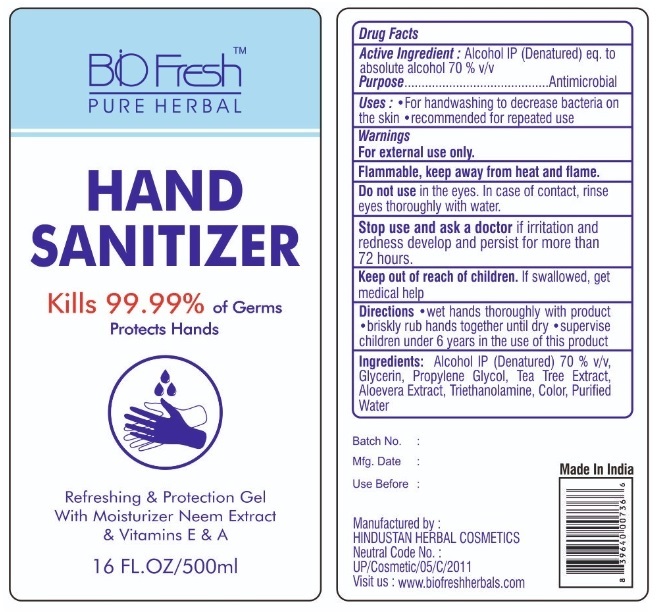 DRUG LABEL: BIOFRESH HAND SANITIZER
NDC: 77104-999 | Form: GEL
Manufacturer: HINDUSTAN HERBAL COSMETICS
Category: otc | Type: HUMAN OTC DRUG LABEL
Date: 20200819

ACTIVE INGREDIENTS: ALCOHOL 70 mL/100 mL
INACTIVE INGREDIENTS: GLYCERIN; PROPYLENE GLYCOL; MELALEUCA ALTERNIFOLIA LEAF; ALOE VERA LEAF; TROLAMINE; WATER

Bio FreshTM PURE HERBAL HAND SANITIZER

Active Ingredient :

Alcohol IP (Denatured) eq. to absolute alcohol 70% v/v

Purpose

Antimicrobial

INDICATIONS AND USAGE

Uses: • For handwashing to decrease bacteria on the skin • recommended for repeated use

Warnings

For external use only.

Flammable, Keep away from heat or flame.

Do not use in the eyes. In case of contact, rinse eyes thoroughly with water.

Stop use and ask a doctor if irritation and redness develop and persist for more than 72 hours.

Keep out of reach of children. If swallowed, get medical help

DOSAGE AND ADMINISTRATION

Directions • wet hands thoroughly with product • briskly rub hands together until dry • supervise children under 6 years in the use of this product

INACTIVE INGREDIENT

Ingredients: Alcohol IP (Denatured) 70% v/v, Glycerin, Propylene Glycol, Tea Tree Extract, Aloevera Extract, Triethanolamine, Color, Purified Water

Kills 99.99% of Germs

Protects Hands

Refreshing & Protection Gel

With Moisturizer Neem Extract & Vitamins E & A

Manufactured by :

HINDUSTAN HERBAL COSMETICS

Visit us : www.biofreshherbals.com

Made In India